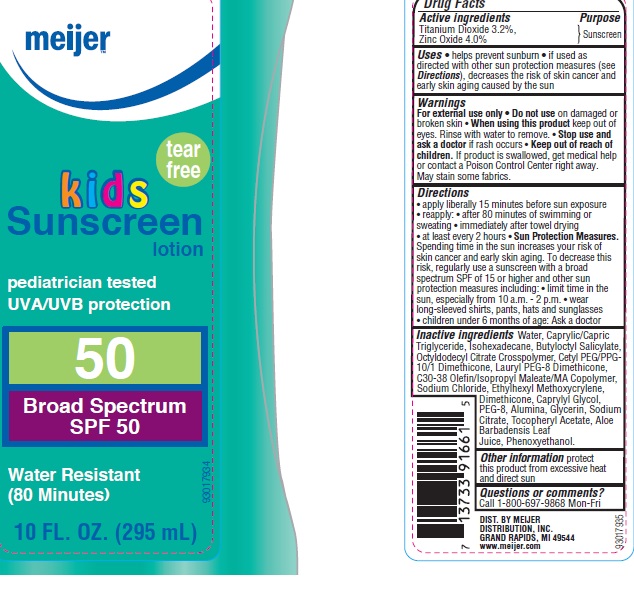 DRUG LABEL: Meijer Kids Tear Free SPF 50
NDC: 41250-922 | Form: LOTION
Manufacturer: Meijer Distribution, Inc.
Category: otc | Type: HUMAN OTC DRUG LABEL
Date: 20160602

ACTIVE INGREDIENTS: TITANIUM DIOXIDE 3.2 g/100 g; ZINC OXIDE 4 g/100 g
INACTIVE INGREDIENTS: WATER; MEDIUM-CHAIN TRIGLYCERIDES; ISOHEXADECANE; BUTYLOCTYL SALICYLATE; SODIUM CHLORIDE; ETHYLHEXYL METHOXYCRYLENE; DIMETHICONE; PHENOXYETHANOL; CAPRYLYL GLYCOL; POLYETHYLENE GLYCOL 400; ALUMINUM OXIDE; GLYCERIN; SODIUM CITRATE, UNSPECIFIED FORM; .ALPHA.-TOCOPHEROL ACETATE; ALOE VERA LEAF

Drug Facts

Active ingredients

Titanium Dioxide 3.2%, Zinc Oxide 4.0%

Purpose

Sunscreen

Uses

- helps prevent sunburn
- if used as directed with other sun protection measures (see Directions), decreases the risk of skin cancer and early skin aging caused by the sun

Warnings

For external use only

Do not use

on damaged or broken skin

When using this product

keep out of eyes. Rinse with water to remove.

Stop use and ask a doctor

if rash occurs

Keep out of reach of children.

If product is swallowed, get medical help or contact a Poison Control Center right away.

- May stain some fabrics

Directions

- apply liberally 15 minutes before sun exposure
- reapply:
- after 80 minutes of swimming or sweating
- immediately after towel drying
- at least every 2 hours
- Sun Protection Measures: Spending time in the sun increases your risk of skin cancer and early skin aging. To decrease this risk, regularly use a sunscreen with a broad spectrum SPF of 15 or higher and other sun protection measures including:
- limit time in the sun, especially from 10 a.m. to 2 p.m.
- wear long-sleeved shirts, pants, hats and sunglasses
- children under 6 months of age: Ask a doctor

Inactive ingredients

Water, Caprylic/Capric Triglyceride, Isohexadecane, Butyloctyl Salicylate, Octyldodecyl Citrate Crosspolymer, Cetyl PEG/PPG-10/1 Dimethicone, Lauryl PEG-8 Dimethicone, C30-38 Olefin/Isopropyl Maleate/MA Copolymer, Sodium Chloride, Ethylhexyl Methoxycrylene, Dimethicone, Phenoxyethanol, Caprylyl Glycol, PEG-8, Alumina, Glycerin, Sodium Citrate, Tocopheryl Acetate, Aloe Barbadensis Leaf Juice.

Other information

protect this product from excessive heat and direct sun

Questions or comments?

Call 1-800-697-9868 Mon-Fri

Principle Display Label

NDC: 41250-922-57

meijer

tear free

kids

Sunscreen lotion

pediatrician tested

UVA/UVB protection

50

Broad Spectrum

SPF 50

Water Resistant

(80 minutes)

1 FL. OZ. (295 mL)